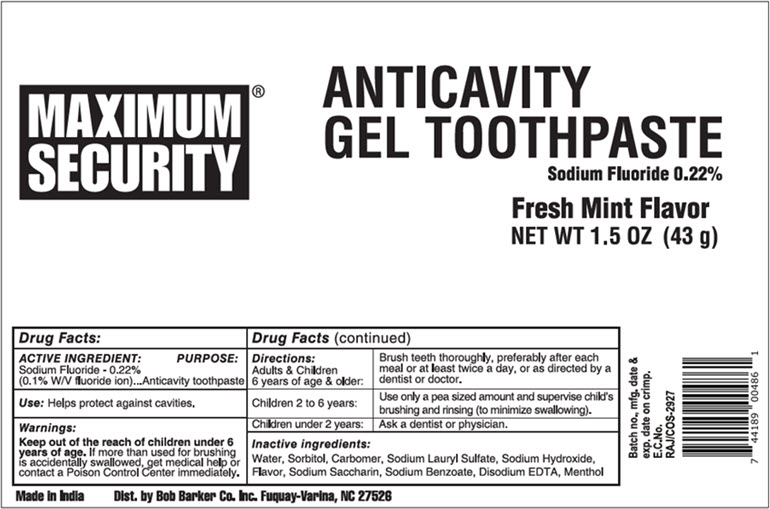 DRUG LABEL: Maximum Security
NDC: 53247-143 | Form: GEL, DENTIFRICE
Manufacturer: Bob Barker Company Inc.
Category: otc | Type: HUMAN OTC DRUG LABEL
Date: 20251020

ACTIVE INGREDIENTS: Sodium Fluoride 2.2 mg/1 g
INACTIVE INGREDIENTS: Water; Sorbitol; Carbomer Homopolymer Type C (Allyl Pentaerythritol Crosslinked); Sodium Lauryl Sulfate; Sodium Hydroxide; SACCHARIN SODIUM; Sodium Benzoate; EDETATE DISODIUM; MENTHOL, UNSPECIFIED FORM

Maximum Security®

Drug Facts:

ACTIVE INGREDIENT

Sodium Fluoride - 0.22% (0.1% W/V fluoride ion)

PURPOSE

Anticavity toothpaste

Use

Helps protect against cavities.

Warnings

KEEP OUT OF REACH OF CHILDREN

Keep out of the reach of children under 6 years of age. If more than used for brushing is accidentally swallowed, get medical help or contact a Poison Control Center immediately.

Directions

Adults & Children 6 years of age & older: | Brush teeth thoroughly, preferably after each meal or at least twice a day, or as directed by a dentist or doctor.
Children 2 to 6 years: | Use only a pea sized amount and supervise child's brushing and rinsing (to minimize swallowing).
Children under 2 years: | Ask a dentist or physician.

Inactive ingredients

Water, Sorbitol, Carbomer, Sodium Lauryl Sulfate, Sodium Hydroxide, Flavor, Sodium Saccharin, Sodium Benzoate, Disodium EDTA, Menthol

Dist. by Bob Barker Co. Inc. Fuquay-Varina, NC 27526

PRINCIPAL DISPLAY PANEL - 43 g Tube Label

MAXIMUM®
SECURITY

ANTICAVITY
GEL TOOTHPASTE
Sodium Fluoride 0.22%

Fresh Mint Flavor
NET WT 1.5 OZ (43 g)